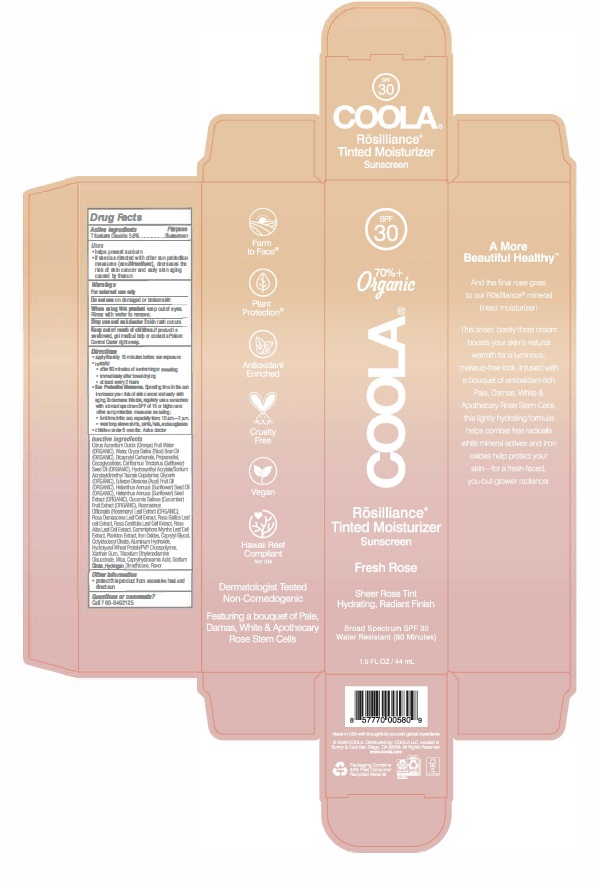 DRUG LABEL: COOLA Rosilliance Mineral Tinted Face Moisturizer SPF 30 Fresh Rose
NDC: 79753-046 | Form: LOTION
Manufacturer: COOLA, LLC
Category: otc | Type: HUMAN OTC DRUG LABEL
Date: 20240522

ACTIVE INGREDIENTS: TITANIUM DIOXIDE 5.6 g/100 mL
INACTIVE INGREDIENTS: DICAPRYLYL CARBONATE; ROSEMARY; XANTHAN GUM; ORANGE; ROSA X ALBA FLOWER OIL; CAPRYLYL GLYCOL; SAFFLOWER OIL; CAPRYLHYDROXAMIC ACID; PROPANEDIOL; FERRIC OXIDE YELLOW; ROSA CENTIFOLIA WHOLE; ACAI OIL; SUNFLOWER OIL; CUCUMBER; POVIDONE, UNSPECIFIED; ROSA DAMASCENA FLOWER; COCO-GLYCERIDES; TRISODIUM ETHYLENEDIAMINE DISUCCINATE; RICE BRAN OIL; ALUMINUM HYDROXIDE; ROSA GALLICA FLOWER; FERRIC OXIDE RED; FERROSOFERRIC OXIDE; WATER; HYDROXYETHYL ACRYLATE/SODIUM ACRYLOYLDIMETHYL TAURATE COPOLYMER (100000 MPA.S AT 1.5%); MICA; HYDROLYZED WHEAT PROTEIN (ENZYMATIC, 3000 MW); GLYCERIN; COMMIPHORA MYRRHA WHOLE; SUNFLOWER SEED; OCTYLDODECYL OLEATE; SODIUM CITRATE

COOLA Rosilliance Mineral Tinted Face Moisturizer SPF 30 - Fresh Rose

ACTIVE INGREDIENT

Titanium Dioxide - 5.6%

PURPOSE

Sunscreen

Uses

- Helps prevent sunburn
- If used as directed with other sun protection measures (see Directions), decreases the risk of skin cancer and early skin aging caused by the sun

WARNINGS

- For external use only
- Do not use on damaged or broken skin
- When using this product keep out of eyes. Rinse with water to remove.
- Stop use and ask a doctor if skin rash occurs.

Keep out of reach of children. If product is swallowed, get medical help or contact a Poison Control Center right away.

Directions

- Apply liberally 15 minutes before sun exposure
- Reapply: • After 80 minutes of swimming or sweating. • Immediately after towel drying • At least every 2 hours
- Sun Protection Measure: Spending time in the sun increases your risk of skin cancer and early skin aging. To decrease this risk, regularly use a sunscreen with a broad spectrum SPF value of 15 or higher and other sun protection measures including:
  • Limit time in the sun, especially from 10 a.m. to 2 p.m.
  • Wear long-sleeved shirts, pants, hats, and sun glasses.

INACTIVE INGREDIENT

Citrus Aurantium Dulcis (Orange) Fruit Water (ORGANIC), Water, Oryza Sativa (Rice) Bran Oil (ORGANIC), Dicaprylyl Carbonate, Propanediol, Cocoglycerides, Carthamus Tinctorius (Safflower) Seed Oil (ORGANIC), Hydroxyethyl Acrylate/Sodium Acryloyldimethyl Taurate Copolymer, Euterpe Oleracea (Acai) Fruit Oil (ORGANIC), Helianthus Annuus (Sunflower) Seed Oil (ORGANIC), Helianthus Annuus (Sunflower) Seed Extract (ORGANIC), Cucumis Sativus (Cucumber) Fruit Extract (ORGANIC), Rosmarinus Officinalis (Rosemary) Leaf Extract (ORGANIC), Rosa Damascena Leaf Cell Extract, Rosa Gallica Flower Extract, Rosa Centifolia Leaf Cell Extract, Rosa Alba Leaf Cell Extract, Commiphora Myrrha Leaf Cell Extract, Plankton Extract, Glycerin (ORGANIC), Iron Oxides, Caprylyl Glycol, Octyldodecyl Oleate, Aluminum Hydroxide, Hydrolyzed Wheat Protein/PVP Crosspolymer, Xanthan Gum, Trisodium Ethylenediamine Disuccinate, Mica, Caprylhydroxamic Acid, Sodium Citrate, Hydrogen Dimethicone, Flavor

OTHER SAFETY INFORMATION

- Protect this product from excessive heat and direct sun

QUESTIONS

Call 760-940-2125